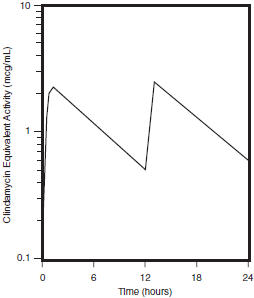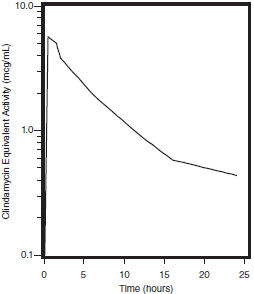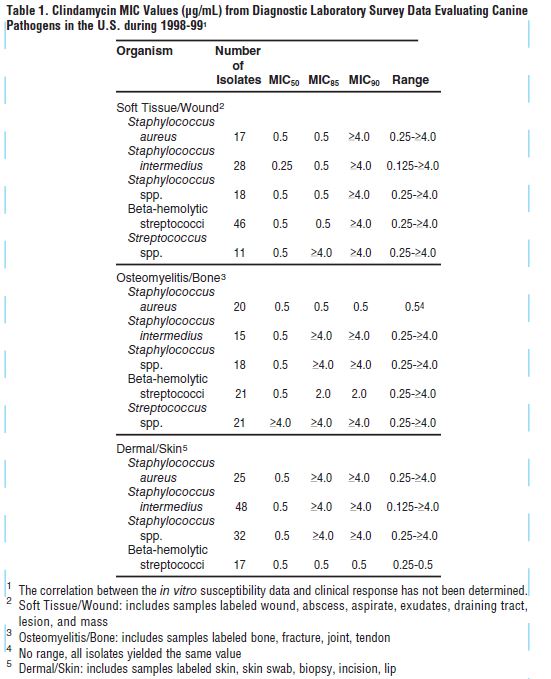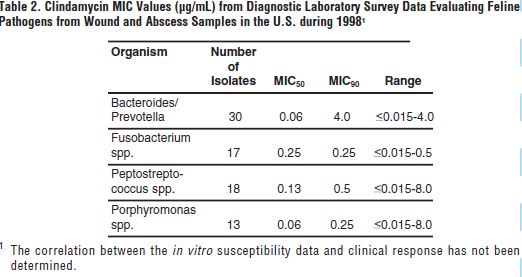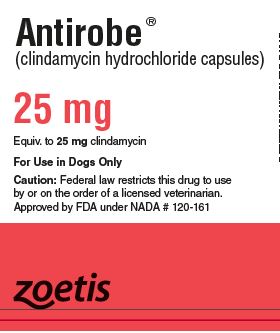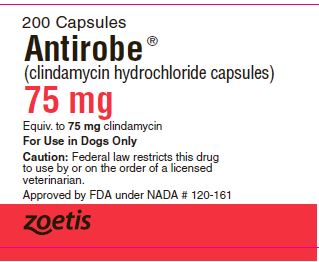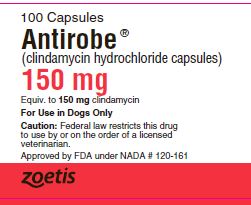 DRUG LABEL: Antirobe
NDC: 54771-3043 | Form: CAPSULE
Manufacturer: Zoetis Inc.
Category: animal | Type: PRESCRIPTION ANIMAL DRUG LABEL
Date: 20230206

ACTIVE INGREDIENTS: CLINDAMYCIN HYDROCHLORIDE 25 mg/1 1

Antirobe®
clindamycin capsules (as clindamycin hydrochloride)
Antirobe® Aquadrops®
clindamycin oral solution (as clindamycin hydrochloride)

Caution

Federal law restricts this drug to use by or on the order of a licensed veterinarian.

DESCRIPTION

ANTIROBE Capsules and ANTIROBE AQUADROPS oral solution contain clindamycin hydrochloride which is the hydrated salt of clindamycin. Clindamycin is a semisyn-thetic antibiotic produced by a 7(S)-chlorosubstitution of the 7(R)-hydroxyl group of a naturally produced antibiotic produced by Streptomyces lincolnensis var. lincolnensis.

ANTIROBE Capsules (For Use in Dogs Only):

25 mg Capsule, each yellow and white capsule contains clindamycin hydrochloride equivalent to 25 mg of clindamycin.

75 mg Capsule, each dark green and white capsule contains clindamycin hydrochloride equivalent to 75 mg of clindamycin.

150 mg Capsule, each white capsule contains clindamycin hydrochloride equivalent to 150 mg of clindamycin.

ANTIROBE AQUADROPS oral solution (For Use in Dogs and Cats) is a palatable formulation intended for oral administration. Each mL of ANTIROBE AQUADROPS oral solution contains clindamycin hydrochloride equivalent to 25 mg clindamycin; and ethyl alcohol, 8.64%.

CLINICAL PHARMACOLOGY

Absorption

Clindamycin hydrochloride is rapidly absorbed from the canine and feline gastrointestinal tract.

Dog Serum Levels

Serum levels at or above 0.5 µg/mL can be maintained by oral dosing at a rate of 2.5 mg/lb of clindamycin hydrochloride every 12 hours. This same study revealed that average peak serum concentrations of clindamycin occur 1 hour and 15 minutes after oral dosing. The elimination half-life for clindamycin in dog serum was approximately 5 hours. There was no bioactivity accumulation after a regimen of multiple oral doses in healthy dogs.

Clindamycin Serum Concentrations
2.5 mg/lb (5.5 mg/kg) After B.I.D. Oral
Dose of Antirobe Capsules to Dogs

Cat Serum Levels

Serum levels at or above 0.5 μg/mL can be maintained by oral dosing at a rate of 5 mg/lb of clindamycin hydrochloride liquid every 24 hours. The average peak serum concentration of clindamycin occurs approximately 1 hour after oral dosing. The elimination half-life of clindamycin in feline serum is approximately 7.5 hours. In healthy cats, minimal accumulation occurs after multiple oral doses of clindamycin hydrochloride, and steady-state should be achieved by the third dose.

Clindamycin Serum Concentrations
5 mg/lb (11 mg/kg) After Single Oral
Dose of Antirobe Aquadrops to Cats

Metabolism and Excretion

Extensive studies of the metabolism and excretion of clindamycin hydrochloride administered orally in animals and humans have shown that unchanged drug and bioactive and bioinactive metabolites are excreted in urine and feces. Almost all of the bioactivity detected in serum after ANTIROBE product administration is due to the parent molecule (clindamycin). Urine bioactivity, however, reflects a mixture of clindamycin and active metabolites, especially N-demethyl clindamycin and clindamycin sulfoxide.

Site and Mode of Action

Clindamycin is an inhibitor of protein synthesis in the bacterial cell. The site of binding appears to be in the 5OS sub-unit of the ribosome. Binding occurs to the soluble RNA fraction of certain ribosomes, thereby inhibiting the binding of amino acids to those ribosomes. Clindamycin differs from cell wall inhibitors in that it causes irreversible modification of the protein-synthesizing subcellular elements at the ribosomal level.

Microbiology

Clindamycin is a lincosaminide antimicrobial agent with activity against a wide variety of aerobic and anaerobic bacterial pathogens. Clindamycin is a bacteriostatic compound that inhibits bacterial protein synthesis by binding to the 5OS ribosomal sub-unit. The minimum inhibitory concentrations (MICs) of Gram-positive and obligate anaerobic pathogens isolated from dogs and cats in the United States are presented in Table 1 and Table 2. Bacteria were isolated in 1998-1999. All MICs were performed in accordance with the Clinical and Laboratory Standards Institute (CLSI).

Table 1
table 2

INDICATIONS

ANTIROBE (brand of clindamycin hydrochloride) Capsules (for use in dogs only) and AQUADROPS Liquid (for use in dogs and cats) are indicated for the treatment of infections caused by susceptible strains of the designated microorganisms in the specific conditions listed below:

Dogs: Skin infections (wounds and abscesses) due to coagulase positive staphylococci (Staphylococcus aureus or Staphylococcus intermedius).

Deep wounds and abscesses due to Bacteroides fragilis, Prevotella melaninogenicus, Fusobacterium necrophorum and Clostridium perfringens.

Dental infections due to Staphylococcus aureus, Bacteroides fragilis, Prevotella melaninogenicus, Fusobacterium necrophorum and Clostridium perfringens.

Osteomyelitis due to Staphylococcus aureus, Bacteroides fragilis, Prevotella melaninogenicus, Fusobacterium necrophorum and Clostridium perfringens.

Cats: Deep wounds and abscesses due to Staphylococcus aureus, Staphylococcus intermedius, Streptococcus spp.

Deep wounds and infections due to Clostridium perfringens and Bacteroides fragilis.

Dental infections due to Staphylococcus aureus, Staphylococcus intermedius, Streptococcus spp., Clostridium perfringens and Bacteroides fragilis.

CONTRAINDICATIONS

ANTIROBE Capsules and ANTIROBE AQUADROPS oral solution are contraindicated in animals with a history of hypersensitivity to preparations containing clindamycin or lincomycin.

Because of potential adverse gastrointestinal effects, do not administer to rabbits, hamsters, guinea pigs, horses, chinchillas or ruminating animals.

WARNINGS

Keep out of reach of children. Not for human use.

PRECAUTIONS

During prolonged therapy of one month or greater, periodic liver and kidney function tests and blood counts should be performed.

The use of ANTIROBE occasionally results in overgrowth of non-susceptible organisms such as clostridia and yeasts. Therefore, the administration of ANTIROBE should be avoided in those species sensitive to the gastrointestinal effects of clindamycin (see CONTRAINDICATIONS). Should superinfections occur, appropriate measures should be taken as indicated by the clinical situation.

Patients with very severe renal disease and/or very severe hepatic disease accompanied by severe metabolic aberrations should be dosed with caution, and serum clindamycin levels monitored during high-dose therapy.

Clindamycin hydrochloride has been shown to have neuromuscular blocking properties that may enhance the action of other neuromuscular blocking agents. Therefore, ANTIROBE should be used with caution in animals receiving such agents.

Safety in gestating bitches and queens or breeding male dogs and cats has not been established.

ADVERSE REACTIONS

Side effects occasionally observed in either clinical trials or during clinical use were vomiting and diarrhea.

To report a suspected adverse reaction call 1-888-963-8471.

DOSAGE AND ADMINISTRATION

Dogs: Infected Wounds, Abscesses, and Dental Infections

Oral: 2.5-15.0 mg/lb body weight every 12 hours

Duration: Treatment with ANTIROBE products may be continued up to a maximum of 28 days if clinical judgment indicates. Treatment of acute infections should not be continued for more than three or four days if no response to therapy is seen

Dosage Schedule

Capsules
ANTIROBE 25 mg, administer 1-6 capsules every 12 hours for each 10 pounds of body weight.
ANTIROBE 75 mg, administer 1-6 capsules every 12 hours for each 30 pounds of body weight.
ANTIROBE 150 mg, administer 1-6 capsules every 12 hours for each 60 pounds of body weight.

Oral Solution
ANTIROBE AQUADROPS, administer 1-6 mL/10 lbs body weight every 12 hours.

Dogs: Osteomyelitis

Oral: 5.0-15.0 mg/lb body weight every 12 hours

Duration: Treatment with ANTIROBE is recommended for a minimum of 28 days. Treatment should not be continued for longer than 28 days if no response to therapy is seen.

Dosage Schedule:
Capsules
ANTIROBE 25 mg, administer 2-6 capsules every 12 hours for each 10 pounds of body weight.
ANTIROBE 75 mg, administer 2-6 capsules every 12 hours for each 30 pounds of body weight.
ANTIROBE 150 mg, administer 2-6 capsules every 12 hours for each 60 pounds of body weight.

Oral Solution
ANTIROBE AQUADROPS, administer 2-6 mL/10 lbs body weight every 12 hours.

Cats:
Infected Wounds, Abscesses, and Dental Infections 5.0 - 15.0 mg/lb body weight once every 24 hours depending on the severity of the condition.

Duration: Treatment with ANTIROBE AQUADROPS oral solution may be continued up to a maximum of 14 days if clinical judgment indicates. Treatment of acute infections should not be continued for more than three to four days if no clinical response to therapy is seen

Dosage schedule:

ANTIROBE AQUADROPS, to provide 5.0 mg/lb, administer 1 mL/5 lbs body weight once every 24 hours; to provide 15.0 mg/lb, administer 3 mL/5 lbs body weight once every 24 hours.

ANIMAL SAFETY SUMMARY

Rat and Dog Data: One year oral toxicity studies in rats and dogs at doses of 30, 100 and 300 mg/kg/day (13.6, 45.5 and 136.4 mg/lb/day) have shown clindamycin hydrochloride capsules to be well tolerated. Differences did not occur in the parameters evaluated to assess toxicity when comparing groups of treated animals with contemporary controls. Rats administered clindamycin hydrochloride at 600 mg/kg/day (272.7 mg/lb/day) for six months tolerated the drug well; however, dogs orally dosed at 600 mg/kg/day (272.7 mg/lb/day) vomited, had anorexia, and subsequently lost weight. At necropsy these dogs had erosive gastritis and focal areas of necrosis of the mucosa of the gallbladder.

Safety in gestating bitches or breeding males has not been established.

Cat Data: The recommended daily therapeutic dose range for clindamycin hydrochloride (ANTIROBE AQUADROPS oral solution) is 11 to 33 mg/kg/day (5 to 15 mg/lb/day) depending on the severity of the condition. Clindamycin hydrochloride (ANTIROBE AQUADROPS oral solution) was tolerated with little evidence of toxicity in domestic shorthair cats when administered orally at 10X the minimum recommended therapeutic daily dose (11 mg/kg; 5 mg/lb) for 15 days, and at doses up to 5X the minimum recommended therapeutic dose for 42 days. Gastrointestinal tract upset (soft feces to diarrhea) occurred in control and treated cats with emesis occurring at doses 3X or greater than the minimum recommended therapeutic dose (11 mg/kg/day; 5 mg/lb/day). Lymphocytic inflammation of the gallbladder was noted in a greater number of treated cats at the 110 mg/kg/day (50 mg/lb/day) dose level than for control cats. No other effects were noted. Safety in gestating queens or breeding male cats has not been established.

STORAGE

Store at controlled room temperature 20° to 25°C (68° to 77°F).

HOW SUPPLIED

ANTIROBE Capsules are available as:
25 mg - bottles of 600
75 mg - bottles of 200
150 mg - bottles of 100.
Approved by FDA under NADA # 120-161
ANTIROBE AQUADROPS oral solution is available as 20 mL filled in 30 mL bottles (25 mg/mL) supplied in packers containing 12 cartoned bottles with direction labels and calibrated dosing droppers.
Approved by FDA under NADA # 135-940

To report suspected adverse events, for technical assistance or to obtain a copy of the Safety Data Sheet (SDS), contact Zoetis Inc. at 1-888-963-8471 or www.zoetis.com.
For additional information about adverse drug experience reporting for animal drugs, contact FDA at 1-888-FDA-VETS or online at http://www.fda.gov/reportanimalae.

ANTIROBE AQUADROPS
zoetis
Distributed by:
Zoetis Inc.
Kalamazoo, MI 49007
ANTIROBE Capsules
zoetis
Manufactured by:
Fareva Amboise, France
Distributed by:
Zoetis Inc., Kalamazoo, MI 49007
Product of China
Revised: September 2022